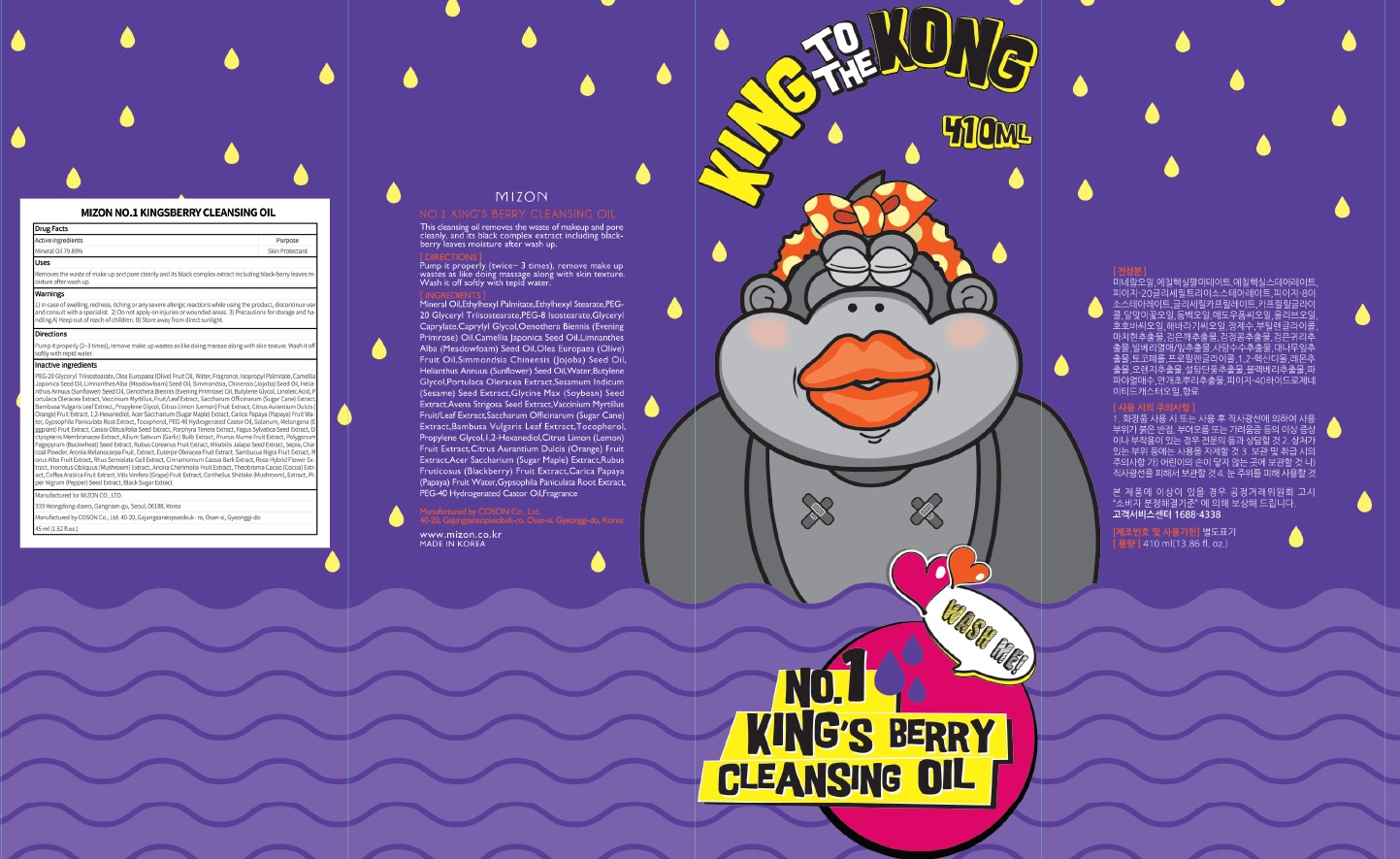 DRUG LABEL: MIZON NO.1 KINGSBERRY CLEANSING OI L
NDC: 57718-300 | Form: OIL
Manufacturer: MIZON CO.,LTD.
Category: otc | Type: HUMAN OTC DRUG LABEL
Date: 20180724

ACTIVE INGREDIENTS: Mineral Oil 327.54 g/410 mL
INACTIVE INGREDIENTS: Water; Isopropyl Palmitate

ACTIVE INGREDIENT

Active ingredients: Mineral Oil 79.89%

INACTIVE INGREDIENT

Inactive ingredients:

PEG-20 Glyceryl Triisostearate, Olea Europaea (Olive) Fruit Oil, Water, Fragrance, Isopropyl Palmitate, Camellia Japonica Seed Oil, Limnanthes Alba (Meadowfoam) Seed Oil, Simmondsia Chinensis (Jojoba) Seed Oil, Helianthus Annuus (Sunflower) Seed Oil, Oenothera Biennis (Evening Primrose) Oil, Butylene Glycol, Linoleic Acid, Portulaca Oleracea Extract, Vaccinium Myrtillus Fruit/Leaf Extract, Saccharum Officinarum (Sugar Cane) Extract, Bambusa Vulgaris Leaf Extract, Propylene Glycol, Citrus Limon (Lemon) Fruit Extract, Citrus Aurantium Dulcis (Orange) Fruit Extract, 1,2-Hexanediol, Acer Saccharium (Sugar Maple) Extract, Carica Papaya (Papaya) Fruit Water, Gypsophila Paniculata Root Extract, Tocopherol, PEG-40 Hydrogenated Castor Oil, Solanum Melongena (Eggplant) Fruit Extract, Cassia Obtusifolia Seed Extract, Porphyra Tenera Extract, Fagus Sylvatica Seed Extract, Dictyopteris Membranacea Extract, Allium Sativum (Garlic) Bulb Extract, Prunus Mume Fruit Extract, Polygonum Fagopyrum (Buckwheat) Seed Extract, Rubus Coreanus Fruit Extract, Mirabilis Jalapa Seed Extract, Sepia, Charcoal Powder, Aronia Melanocarpa Fruit Extract, Euterpe Oleracea Fruit Extract, Sambucus Nigra Fruit Extract, Morus Alba Fruit Extract, Rhus Semialata Gall Extract, Cinnamomum Cassia Bark Extract, Rosa Hybrid Flower Extract, Inonotus Obliquus (Mushroom) Extract, Anona Cherimolia Fruit Extract, Theobroma Cacao (Cocoa) Extract, Coffea Arabica Fruit Extract, Vitis Vinifera (Grape) Fruit Extract, Corthellus Shiitake (Mushroom) Extract, Piper Nigrum (Pepper) Seed Extract, Black Sugar Extract

PURPOSE

Purpose: Skin Protectant

WARNINGS

1) In case of swelling, redness, itching or any severe allergic reactions while using the product,discontinue use and consult with a specialist. 2) Do not apply on injuries or wounded areas. 3) Precautions for storage and handling A) Keep out of reach of children. B) Store away from direct sunlight.

KEEP OUT OF REACH OF CHILDREN

Uses

Removes the waste of make up and pore cleanly and its black complex extract including black-berry leaves moisture after wash up.

Directions

Pump it properly (2~3 times), remove make up wastes as like doing massae along with skin texture. Wash it off softly with repid water.